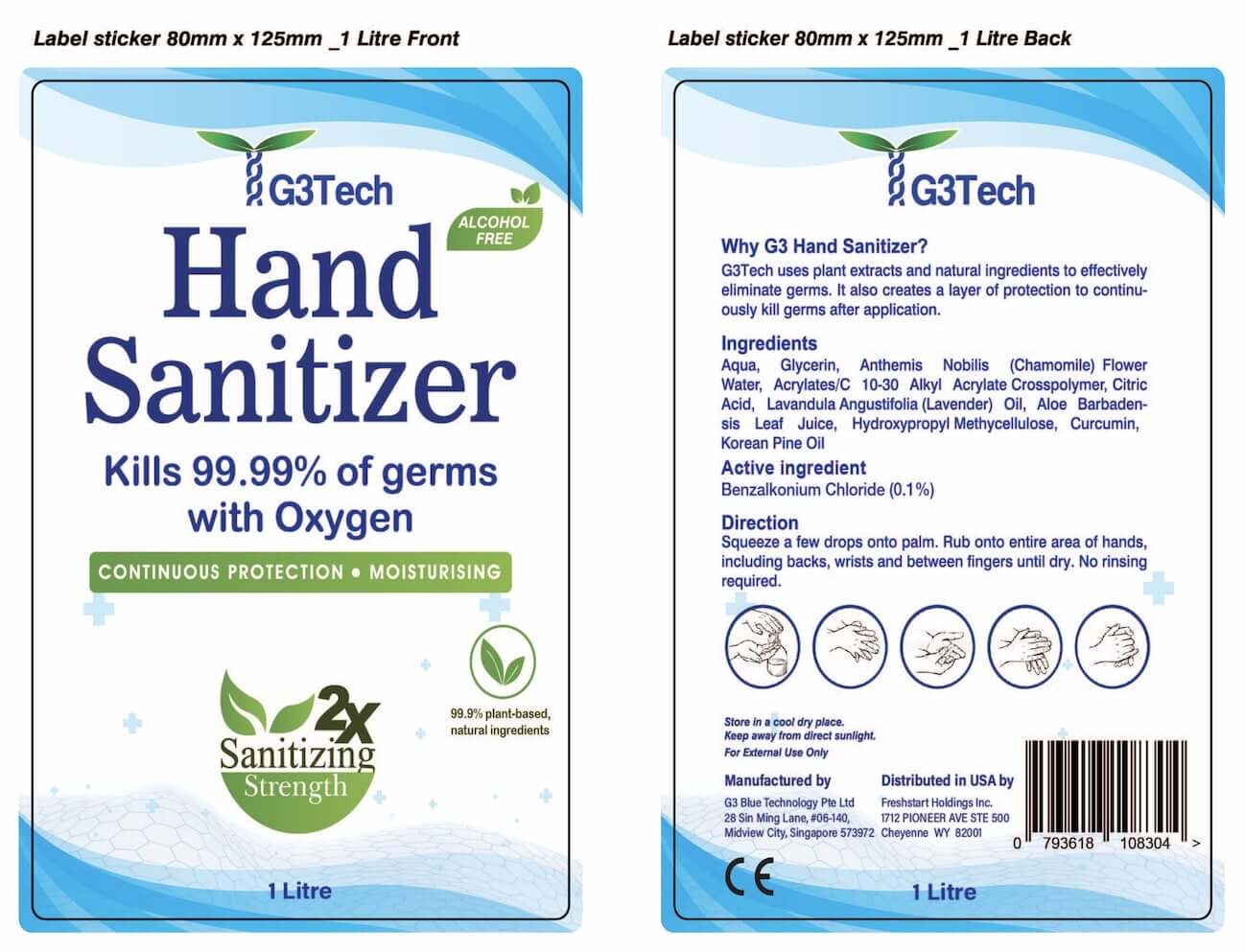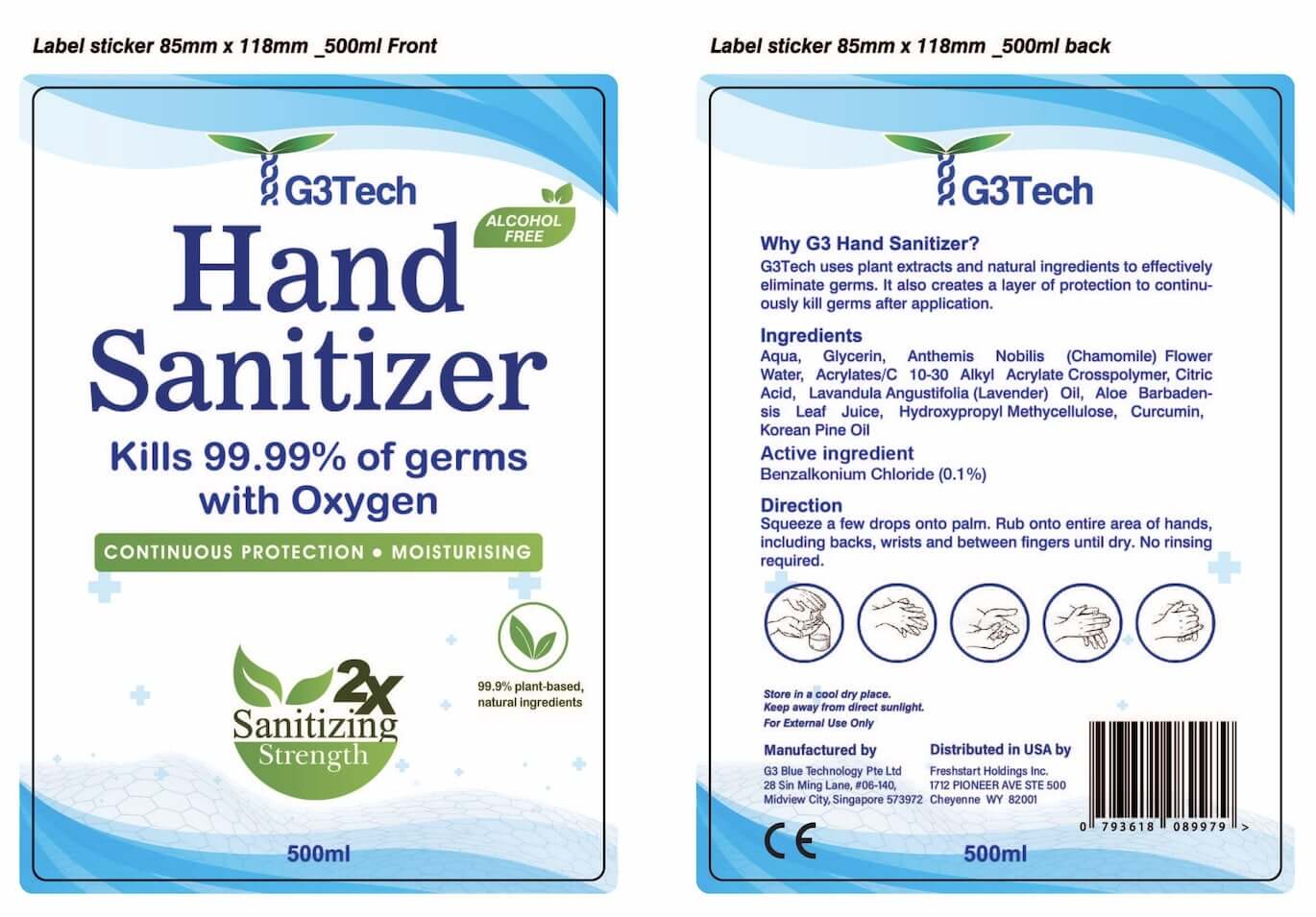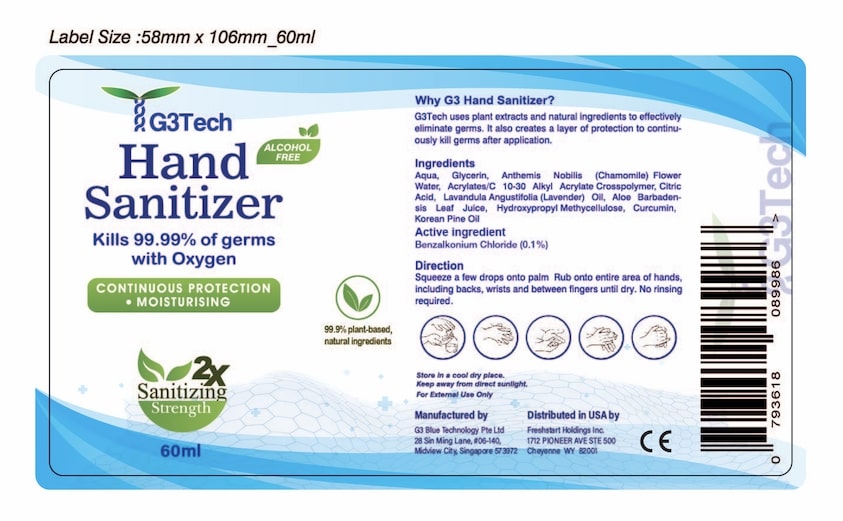 DRUG LABEL: G3Tech Hand Sanitizer
NDC: 79176-001 | Form: GEL
Manufacturer: Freshstart Holdings Inc.
Category: otc | Type: HUMAN OTC DRUG LABEL
Date: 20200917

ACTIVE INGREDIENTS: BENZALKONIUM CHLORIDE 10 mg/100 mL
INACTIVE INGREDIENTS: CITRIC ACID MONOHYDRATE; LAVENDER OIL; ALOE VERA LEAF; GLYCERIN; CURCUMIN; WATER; HYPROMELLOSE, UNSPECIFIED; WHITE PINE OIL; CHAMAEMELUM NOBILE FLOWER OIL; CARBOMER INTERPOLYMER TYPE A (55000 CPS)

Active Ingredient(s)

Benzalkonium Chloride 0.1% v/v. Purpose: Antiseptic

Purpose

Antiseptic, Hand Sanitizer

Use

Hand Sanitizer to help reduce bacteria that potentially can cause disease. For use when soap and water are not available.

Warnings

For External Use Only.

Directions

- Squeeze a few drops onto palm.
- Rub onto entire area of hands, including backs, wirsts and between fingers until dry.
- No rinsing required.

Other information

- Store in a cool dry place
- Keep away from direct sunlight

Inactive ingredients

Aqua,

Glycerin,

Anthemis Nobilis (Chamomile) Flower Water,

Acrylates/C 10-30 Alkyl Acrylate Crosspolymer,

Citric Acid,

Lavandula Angustifolia (Lavender) Oil,

Aloe Barbadensis Leaf Juice,

Hydroxypropyl Methylcellulose,

Curcumin,

Korean Pine Oil

Keep out of reach of children.

Package Label - Principal Display Panel

60ml NDC: 79176-001-01

500ml NDC: 79176-001-02

1000ml NDC: 79176-001-03